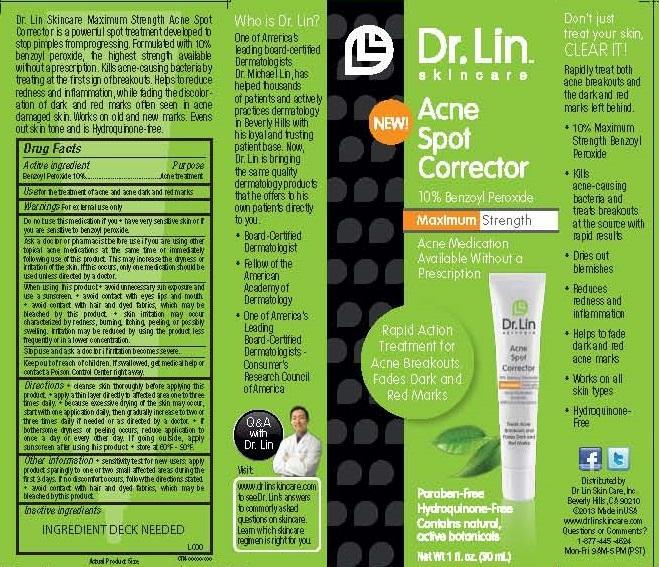 DRUG LABEL: ACNE SPOT CORRECTOR
NDC: 58876-106 | Form: CREAM
Manufacturer: DR LIN SKINCARE
Category: otc | Type: HUMAN OTC DRUG LABEL
Date: 20140711

ACTIVE INGREDIENTS: BENZOYL PEROXIDE 10 g/100 mL
INACTIVE INGREDIENTS: WATER; GLYCERIN; POLYACRYLAMIDE (1500 MW); C13-14 ISOPARAFFIN; LAURETH-7; CALENDULA OFFICINALIS WHOLE; ARBUTIN; KOJIC ACID; ASCORBIC ACID; SODIUM PYRROLIDONE CARBOXYLATE; ALLANTOIN; PANTHENOL; HYALURONATE SODIUM; CALENDULOSIDE E; PHENOXYETHANOL; METHYLISOTHIAZOLINONE

ACTIVE INGREDIENT

BENZYL PEROXIDE 10%

PURPOSE

ACNE TREATMENT

USE

FOR THE TREATMENT OF ACNE AND ACNE DARK AND RED MARKS.

WARNINGS

FOR EXTERNAL USE ONLY

WHEN USING THIS PRODUCT

- AVOID UNNECESSARY SUN EXPOSURE AND USE A SUNSCREEN
- AVOID CONTACT WTH EYES, LIPS AND MOUTH.
- AVOID CONTACT WITH HAIR AND DYED FABRICS, WHICH MAY BE BLEACHED BY THIS PRODUCT.
- SKIN IRRITATION MAY OCCUR CHARACTERIZED BY REDNESS, BURNING, TCHING, PEELING, OR POSSIBLY SWELLING. IRRITATION MAY BE REDUCED BY USING THE PRODUCT LESS FREQUEBTLY OR IN A LOWER CONCENTRATION.

DO NOT USE THIS MEDICATION IF YOU

- HAVE VERY SENSITIVE SKIN OR IF YOU ARE SENSITIVE TO BENZOYL PEROXIDE.

ASK A DOCTOR OR PHARMACIST BEFORE USE IF YOU ARE USING OTHER TOPICAL ACNE MEDICATIONS AT THE SAME TIME OR IMMEDIATELY FOLLOWING USE OF THIS PRODUCT. THIS MAY INCREASE DRYNESS OR IRRITATION OF THE SKIN. IF THIS OCCURS, ONLY ONE MEDICATION SHOULD BE USED UNLESS DIRECTED BY A DOCTOR.

Other information

• sensitivity test: apply product sparingly to one or two small affected areas during the first 3 days. If no discomfort occurs, follow the directions stated.

• avoid contact with hair and dyed fabrics, which may be bleached by this product.

STOP USE AND ASK A DOCTOR IF IRRITATION BECOMES SEVERE.

KEEP OUT OF REACH OF CHILDREN. IF PRODUCT IS SWALLOWED, GET MEDICAL HELP OR CONTACT A POISON CONTROL CENTER RIGHT AWAY.

DIRECTIONS

- CLEANSE SKIN THOROUGHLY BEFORE APPLYING THIS PRODUCT.
- APPLY A THIN LAYER DIRECTLY TO AFFECTED AREA ONE TO THREE TIMES DAILY.
- BECAUSE EXCESSIVE DRYING OF THE SKIN MAY OCCUR, START WITH ONE APPLICATION DAILY, THEN GRADUALLY INCREASE TO TWO OR THREE TIMES DAILY IF NEEDED OR AS DIRECTED BY A DOCTOR.
- IF BOTHERSOME DRYNESS OR PEELING CCURS, REDUCE APPLICATION TO ONCE A DAY OR EVERY OTHER DAY.
- IF GOING OUTSIDE, APPLY SUNSCREEN AFTER USING THIS PRODUCT.
- STORE AT 60°F - 90°F.

INACTIVE INGREDIENTS

Water, Glycerin, Polyacrylamide, C13-14 Isoparaffin, Laureth-7, Calendula Extract, Arbutin, Kojic Acid, Ascorbic Acid, Sodium PCA, Allantoin, Panthenol, Sodium Hyaluronate, Glycosphingolipids, Phenoxyethanol, Methylisothiazolinone, Fragrance

QUESTIONS OR COMMENTS?

1-877-445-4624

MON-FRI 8AM - 5PM (PST)